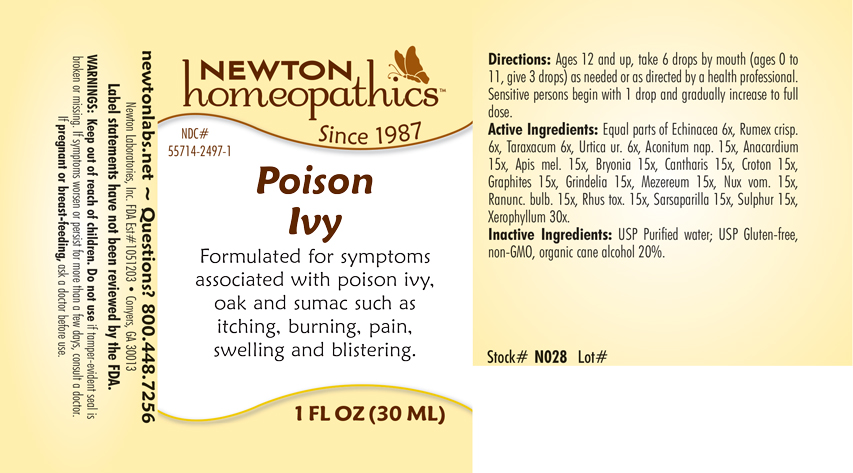 DRUG LABEL: Poison Ivy
NDC: 55714-2497 | Form: LIQUID
Manufacturer: Newton Laboratories, Inc.
Category: homeopathic | Type: HUMAN OTC DRUG LABEL
Date: 20250207

ACTIVE INGREDIENTS: XEROPHYLLUM ASPHODELOIDES 30 [hp_X]/1 mL; ACONITUM NAPELLUS 15 [hp_X]/1 mL; SEMECARPUS ANACARDIUM JUICE 15 [hp_X]/1 mL; APIS MELLIFERA 15 [hp_X]/1 mL; BRYONIA ALBA ROOT 15 [hp_X]/1 mL; LYTTA VESICATORIA 15 [hp_X]/1 mL; CROTON TIGLIUM SEED 15 [hp_X]/1 mL; GRAPHITE 15 [hp_X]/1 mL; GRINDELIA HIRSUTULA FLOWERING TOP 15 [hp_X]/1 mL; DAPHNE MEZEREUM BARK 15 [hp_X]/1 mL; STRYCHNOS NUX-VOMICA SEED 15 [hp_X]/1 mL; RANUNCULUS BULBOSUS 15 [hp_X]/1 mL; TOXICODENDRON PUBESCENS LEAF 15 [hp_X]/1 mL; SMILAX ORNATA ROOT 15 [hp_X]/1 mL; SULFUR 15 [hp_X]/1 mL; ECHINACEA, UNSPECIFIED 6 [hp_X]/1 mL; RUMEX CRISPUS ROOT 6 [hp_X]/1 mL; TARAXACUM OFFICINALE 6 [hp_X]/1 mL; URTICA URENS 6 [hp_X]/1 mL
INACTIVE INGREDIENTS: ALCOHOL; WATER

Poison 2497L

INDICATIONS & USAGE SECTION

Formulated for symptoms associated with poison ivy, oak and sumac such as itching, burning, pain, swelling and blistering.

DOSAGE & ADMINISTRATION SECTION

Directions: Ages 12 and up, take 6 drops by mouth (ages 0 to 11, give 3 drops) as needed or as directed by a health professional. Sensitive persons begin with 1 drop and gradually increase to full dose.

OTC - ACTIVE INGREDIENT SECTION

Equal parts of Echinacea 6x, Rumex crispus 6x, Taraxacum officinale 6x, Urtica urens 6x, Aconitum napellus 15x, Anacardium 15x, Apis mellifica 15x, Bryonia 15x, Cantharis 15x, Croton tiglium 15x, Graphites 15x, Grindelia 15x, Mezereum 15x, Nux vomica 15x, Ranunculus bulbosus 15x, Rhus toxicodendron 15x, Sarsaparilla 15x, Sulphur 15x, Xerophyllum asphodeloides 30x.

OTC - PURPOSE SECTION

Formulated for symptoms associated with poison ivy, oak and sumac such as itching, burning, pain, swelling and blistering.

INACTIVE INGREDIENT SECTION

Inactive Ingredients: USP Purified Water; USP Gluten-free, non-GMO, organic cane alcohol 20%.

QUESTIONS SECTION

newtonlabs.net – Questions? 800.448.7256

Newton Laboratories, Inc. FDA Est # 1051203 - Conyers, GA 30013

OTC - PREGNANCY OR BREAST FEEDING SECTION

If pregnant or breast-feeding, ask a doctor before use.

WARNINGS SECTION

WARNINGS: Keep out of reach of children. Do not use if tamper-evident seal is broken or missing. If symptoms worsen or persist for more than a few days, consult a doctor. If pregnant or breast-feeding, ask a doctor before use.

OTC - KEEP OUT OF REACH OF CHILDREN SECTION

Keep out of reach of children.